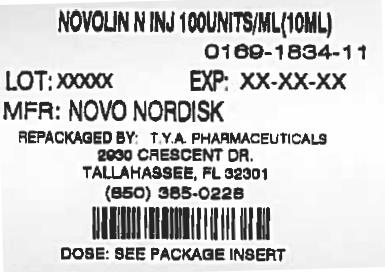 DRUG LABEL: Novolin
                                    
NDC: 64725-1834 | Form: INJECTION, SUSPENSION
Manufacturer: TYA Pharmaceuticals
Category: otc | Type: HUMAN OTC DRUG LABEL
Date: 20130827

ACTIVE INGREDIENTS: INSULIN HUMAN 100 [iU]/1 mL
INACTIVE INGREDIENTS: GLYCERIN; METACRESOL; PHENOL; PROTAMINE SULFATE; SODIUM PHOSPHATE, DIBASIC, DIHYDRATE; HYDROCHLORIC ACID; SODIUM HYDROXIDE; WATER; ZINC CHLORIDE

Novolin N NPH, Human Insulin Isophane Suspension (recombinant DNA origin) 100 units/mL

PATIENT PACKAGE INSERT

Patient Information for Novolin N®

NOVOLIN N (NO-voe-lin)®

NPH,

Human Insulin Isophane Suspension Injection

(recombinant DNA origin) units/mL 100

PURPOSE

Important:

. Do not change the type of insulin you use unless told to do so by your healthcare provider. The amount of insulin you take as well as the best time for you to take your insulin may need to change if you take a different type of insulin. Know your insulin

Make sure that you know the type and strength of insulin that is prescribed for you.

Read the Patient Information leaflet that comes with Novolin N before you start taking it and each time you get a refill. There may be new information. This leaflet does not take the place of talking with your healthcare provider about your diabetes or your treatment. Make sure you know how to manage your diabetes. Ask your healthcare provider if you have any questions about managing your diabetes.®

What is Novolin N?®

Novolin N is a man-made insulin (recombinant DNA origin) NPH, Human Insulin Isophane Suspension that is structurally identical to the insulin produced by the human pancreas that is used to control high blood sugar in patients with diabetes mellitus.®

Who should not use Novolin N?®

Do not take Novolin N if:®

- Your blood sugar is too low (hypoglycemia).
- You are allergic to anything in Novolin N. See the end of this leaflet for a complete list of ingredients in Novolin N. Check with your healthcare provider if you are not sure. ®®

Tell your healthcare provider:

- . Medical conditions can affect your insulin needs and your dose of Novolin N. about all of your medical conditions®
- You and your healthcare provider should talk about the best way to manage your diabetes while you are pregnant or breastfeeding. Novolin N has not been studied in pregnant or nursing women. if you are pregnant or breastfeeding.®
- including prescription and non-prescription medicines, vitamins and herbal supplements. Many medicines can affect your blood sugar levels and your insulin needs. Your Novolin N dose may need to change if you take other medicines. about all of the medicines you take,®
- if you take any other medicines, especially ones commonly called TZDs (thiazolidinediones).
- . If you have heart failure, it may get worse while you take TZDs with Novolin N. if you have heart failure or other heart problems®

Keep a list of your medicines with you to show all your healthcare providers when you get a new medicine. Know the medicines you take.

DOSAGE AND ADMINISTRATION

How should I take Novolin N?®

Only use Novolin N if it appears cloudy or milky. There may be air bubbles. This is normal. If the precipitate (the white deposit at the bottom of the vial) has become lumpy or granular in appearance or has formed a deposit of solid particles on the wall of the vial, do not use it, and call Novo Nordisk at 1-800-727-6500. This insulin should not be used if the liquid in the vial remains clear after the vial has been gently rotated.®

Novolin N comes in:®

- 10 mL vials (small bottles) for use with syringe

INDICATIONS AND USAGE

Talk to your healthcare provider if you have any questions. Your healthcare provider should show you how to inject Novolin N before you start taking it. Follow your healthcare provider’s instructions to make changes to your insulin dose. Read the instructions for use that come with your Novolin N product.®®

- Take Novolin N exactly as prescribed.®
- The effects of Novolin N start working 1½ hours after injection. Novolin N is an intermediate-acting insulin.®®
- The greatest blood sugar lowering effect is between 4 and 12 hours after the injection. This blood sugar lowering may last up to 24 hours.
- any change of insulin should be made cautiously and only under medical supervision. Doses of oral anti-diabetic medicines may also need to change, if your insulin is changed. While using Novolin N,®
- with any insulins other than Regular human insulin in the same syringe. Do not mix Novolin N®
- Novolin N may affect your blood sugar levels sooner if you inject it into the skin of your stomach area. Inject Novolin N into the skin of your stomach area, upper arms, buttocks or upper legs.®® Never inject Novolin N into a vein or into a muscle.®
- Change (rotate) your injection site within the chosen area (for example, stomach or upper arm) with each dose. Do not inject into the same spot for each injection.
- You can treat mild low blood sugar (hypoglycemia) by drinking or eating something sugary right away (fruit juice, sugar candies, or glucose tablets). It is important to treat low blood sugar (hypoglycemia) right away because it could get worse and you could pass out (become unconscious). If you pass out, you will need help from another person or emergency medical services right away, and will need treatment with a glucagon injection or treatment at a hospital. See “What are the possible side effects of Novolin N?” for more information on low blood sugar (hypoglycemia). If you take too much Novolin N, your blood sugar may fall low (hypoglycemia).®®
- If high blood sugar (hyperglycemia) is not treated it can lead to diabetic ketoacidosis, which can lead to serious problems, like loss of consciousness (passing out), coma or even death. Follow your healthcare provider’s instructions for treating high blood sugar (hyperglycemia), and talk to your healthcare provider if high blood sugar is a problem for you. Severe or continuing high blood sugar (hyperglycemia) requires prompt evaluation and treatment by your healthcare provider. Know your symptoms of high blood sugar (hyperglycemia) and diabetic ketoacidosis which may include: If you forget to take your dose of Novolin N, your blood sugar may go too high (hyperglycemia).®

- increased thirst

- fruity smell on breath

- frequent urination and dehydration

- high amounts of sugar and ketones in your urine

- confusion or drowsiness

- nausea, vomiting (throwing up) or stomach pain

- loss of appetite

- a hard time breathing

Ask your healthcare provider how often you should check your blood sugar levels for hypoglycemia (too low blood sugar) and hyperglycemia (too high blood sugar). Check your blood sugar levels.

Your insulin dosage may need to change because of:

- illness

- change in diet

- stress

- change in physical activity or exercise

- other medicines you take

- surgery

See the end of this patient information for instructions about preparing and giving the injection.

What should I avoid while using Novolin N?®

- Alcohol, including beer and wine, may affect your blood sugar when you take Novolin N. Alcohol.®
- You may have difficulty concentrating or reacting if you have low blood sugar (hypoglycemia). Be careful when you drive a car or operate machinery. Ask your healthcare provider if it is alright to drive if you often have: Driving and operating machinery.
  ∘ low blood sugar
  ∘ decreased or no warning signs of low blood sugar

What are the possible side effects of Novolin N?®

- Symptoms of hypoglycemia (low blood sugar) may include: Low blood sugar (hypoglycemia).

- sweating

- trouble concentrating or confusion

- dizziness or lightheadedness

- blurred vision

- shakiness

- slurred speech

- hunger

- anxiety, irritability or mood changes

- fast heart beat

- headache

- tingling of lips and tongue

Severe low blood sugar (hypoglycemia) can cause unconsciousness (passing out), seizures, and death. Know your symptoms of low blood sugar. Follow your healthcare provider’s instructions for treating low blood sugar. Talk to your healthcare provider if low blood sugar is a problem for you.

- a rash over your whole body, have trouble breathing, a fast heartbeat, or sweating. Serious allergic reaction (whole body reaction). Get medical help right away if you develop
- You may get redness, swelling, and itching at the injection site. If you keep having skin reactions, or they are serious, talk to your healthcare provider. You may need to stop using Novolin N and use a different insulin. Do not inject insulin into skin that is red, swollen, or itchy. Reactions at the injection site (local allergic reaction).®
- Change (rotate) where you inject your insulin to help prevent these skin changes from happening. Do not inject insulin into this type of skin. Skin thickens or pits at the injection site (lipodystrophy).
- Swelling of your hands and feet
- Taking certain diabetes pills called thiazolidinediones or “TZDs” with Novolin N may cause heart failure in some people. This can happen even if you have never had heart failure or heart problems before. If you already have heart failure it may get worse while you take TZDs with Novolin N. Your healthcare provider should monitor you closely while you are taking TZDs with Novolin N. Tell your healthcare provider if you have any new or worse symptoms of heart failure including: Heart Failure.®®®
  ∘ shortness of breath
  ∘ swelling of your ankles or feet
  ∘ sudden weight gain
Treatment with TZDs and Novolin N may need to be adjusted or stopped by your healthcare provider if you have new or worse heart failure. ®
- Vision changes
- Low potassium in your blood (hypokalemia)

These are not all of the possible side effects from Novolin N. Ask your healthcare provider or pharmacist for more information.®

Call your doctor for medical advice about side effects. You may report side effects to FDA at 1-800-FDA-1088.

How should I store Novolin N?®

All Unopened Novolin N:®

- ° ° ° ° Keep all unopened Novolin N in the refrigerator between 36® to 46 F (2 to 8 C).
- Do not freeze. Do not use Novolin N if it has been frozen. ®
- If refrigeration is not possible, the unopened vial may be kept at room temperature for up to 6 weeks (42 days), as long as it is kept at or below 77°F (25°C).
- Keep unopened Novolin N in the carton to protect from light. ®

Novolin N in use:®

Vials

- Keep at room temperature below 77°F (25°C) for up to 6 weeks (42 days).
- Keep vials away from direct heat or light.
- Throw away an opened vial after 6 weeks (42 days) of use, even if there is insulin left in the vial.
- Unopened vials can be used until the expiration date on the Novolin N label, if the medicine has been stored in a refrigerator. ®

General advice about Novolin N®

Novolin N is used for the treatment of diabetes only. Medicines are sometimes prescribed for conditions that are not mentioned in the patient leaflet. Do not use Novolin N for a condition for which it was not prescribed. Do not give Novolin N to other people, even if they have the same symptoms you have. It may harm them.®®®

This leaflet summarizes the most important information about Novolin N. If you would like more information about Novolin N or diabetes, talk with your healthcare provider. For more information, call 1-800-727-6500 or visit www.novonordisk-us.com.®®

Helpful information for people with diabetes is published by the American Diabetes Association, 1701 N Beauregard Street, Alexandria, VA 22311 and on www.diabetes.org.

ACTIVE INGREDIENT

Novolin N ingredients include:®

- Human Insulin Isophane Suspension (recombinant DNA origin)

INACTIVE INGREDIENT

- Metacresol
- Zinc chloride
- Glycerol
- Sodium hydroxide
- Hydrochloric acid
- Phenol
- Protamine sulfate
- Disodium phosphate dihydrate
- Water for injections

All Novolin N vials are latex-free.®

Date of issue: March 9, 2013

Version: 6

Novolin and Novo Nordisk are registered trademarks of Novo Nordisk A/S.®®

© 2005-2013 Novo Nordisk

Manufactured by:

Novo Nordisk A/S

DK-2880 Bagsvaerd, Denmark

For information about Novolin N contact:®

Novo Nordisk Inc.

800 Scudders Mill Road

Plainsboro, New Jersey 08536

PATIENT INSTRUCTIONS FOR USE

Novolin N 10 mL vial (100 Units/mL, U-100)®

Before starting, gather all of the supplies that you will need to use for preparing and giving your insulin injection.

Never re-use syringes and needles.

How should I use the Novolin N vial?

1. Check to make sure that you have the correct type of insulin. This is especially important if you use different types of insulin.
2. Look at the vial and the insulin. The insulin should be a cloudy or milky suspension The tamper-resistant cap should be in place before the first use. If the cap had been removed before your first use of the vial, or if the precipitate (the white deposit at the bottom of the vial) has become lumpy or granular in appearance or has formed a deposit of solid particles on the wall of the vial, do not use it, and call Novo Nordisk at 1-800-727-6500. .
3. Wash your hands with soap and water. If you clean your injection site with an alcohol swab, let the injection site dry before you inject. Talk with your healthcare provider about how to rotate injection sites and how to give an injection.
4. If you are using a new vial, pull off the tamper-resistant cap. Wipe the rubber stopper with an alcohol swab.
5. Roll the vial gently 10 times in your hands to mix it. This procedure should be carried out with the vial in a horizontal position. The rolling procedure must be repeated until the suspension appears uniformly white and cloudy. Shaking right before the dose is drawn into the syringe may cause bubbles or froth, which could cause you to draw up the wrong dose of insulin.
6. Pull back the plunger on the syringe until the black tip reaches the marking for the number of units you will inject.
7. Push the needle through the rubber stopper of the vial, and push the plunger all the way in to force air into the vial.
8. Turn the vial and syringe upside down and slowly pull the plunger back to a few units beyond the correct dose.
9. If there are any air bubbles, tap the syringe gently with your finger to raise the air bubbles to the top. Then slowly push the plunger to the marking for your correct dose. This process should move any air bubbles present in the syringe back into the vial.
10. Check to make sure you have the right dose of Novolin N in the syringe.
11. Pull the syringe with needle out of the vial’s rubber stopper.
12. Your doctor should tell you if you need to pinch the skin before inserting the needle. This can vary from patient to patient so it is important to ask your doctor if you did not receive instructions on pinching the skin. Insert the needle into the skin. Press the plunger of the syringe to inject the insulin. When you are finished injecting the insulin, pull the needle out of your skin. You may see a drop of Novolin N at the needle tip. This is normal and has no effect on the dose you just received. If you see blood after you take the needle out of your skin, press the injection site lightly with a piece of gauze or an alcohol wipe. Do not rub the area.
13. After your injection, do not recap the needle. Place used syringes, needles and used insulin vials in a disposable puncture-resistant sharps container, or some type of hard plastic or metal container with a screw on cap such as a detergent bottle or coffee can.
14. Ask your healthcare provider about the right way to throw away used syringes and needles. There may be state or local laws about the right way to throw away used syringes and needles. Do not throw away used needles and syringes in household trash or recycle.

How should I mix Novolin N with Regular human insulin?

Different insulins should be mixed only under instruction from a health care provider. Novolin N should be mixed only when injections with syringes are used. Insulin syringes may vary in the amount of space between the bottom line and the needle (“dead space”), so if you are mixing two types of insulin be sure to discuss any change in the model and brand of syringe you are using with your healthcare provider. Novolin N can be mixed with Regular human insulin right before use. When you are mixing Novolin N insulin with Regular human insulin, always draw the Regular human (clear) insulin into the syringe first. Do not mix Novolin N with any other type of insulin besides Regular human insulin.

1. Add together the doses (total number of units) of Regular human insulin and Novolin N that you need to inject. The total dose will determine the final amount (volume) in the syringe after drawing up both insulins into the syringe. For example, if you need 5 units of Novolin N and 2 units of Regular human insulin, the total dose of insulin in the syringe would be 7 units.
2. Roll the Novolin N vial between your hands until the liquid is equally cloudy throughout.
3. Draw into the syringe the same amount of air as the Novolin N dose. Inject this air into the Novolin N vial and then remove the needle from the vial but do not withdraw any of the Novolin N insulin. (Transferring Novolin N to the Regular human insulin vial will contaminate the Regular human insulin vial and may change how quickly it works.)
4. Draw into the syringe the same amount of air as the Regular human insulin dose. Inject this air into the Regular human insulin vial. With the needle in place, turn the vial upside down and withdraw the correct dose of Regular human insulin. The tip of the needle must be in the Regular human insulin to get the full dose and not an air dose.
5. After withdrawing the needle from the Regular human insulin vial, insert the needle into the Novolin N vial. Turn the Novolin N vial upside down with the syringe and needle still in it. Withdraw the correct dose of Novolin N.
6. Inject right away to avoid changes in how quickly the insulin works.